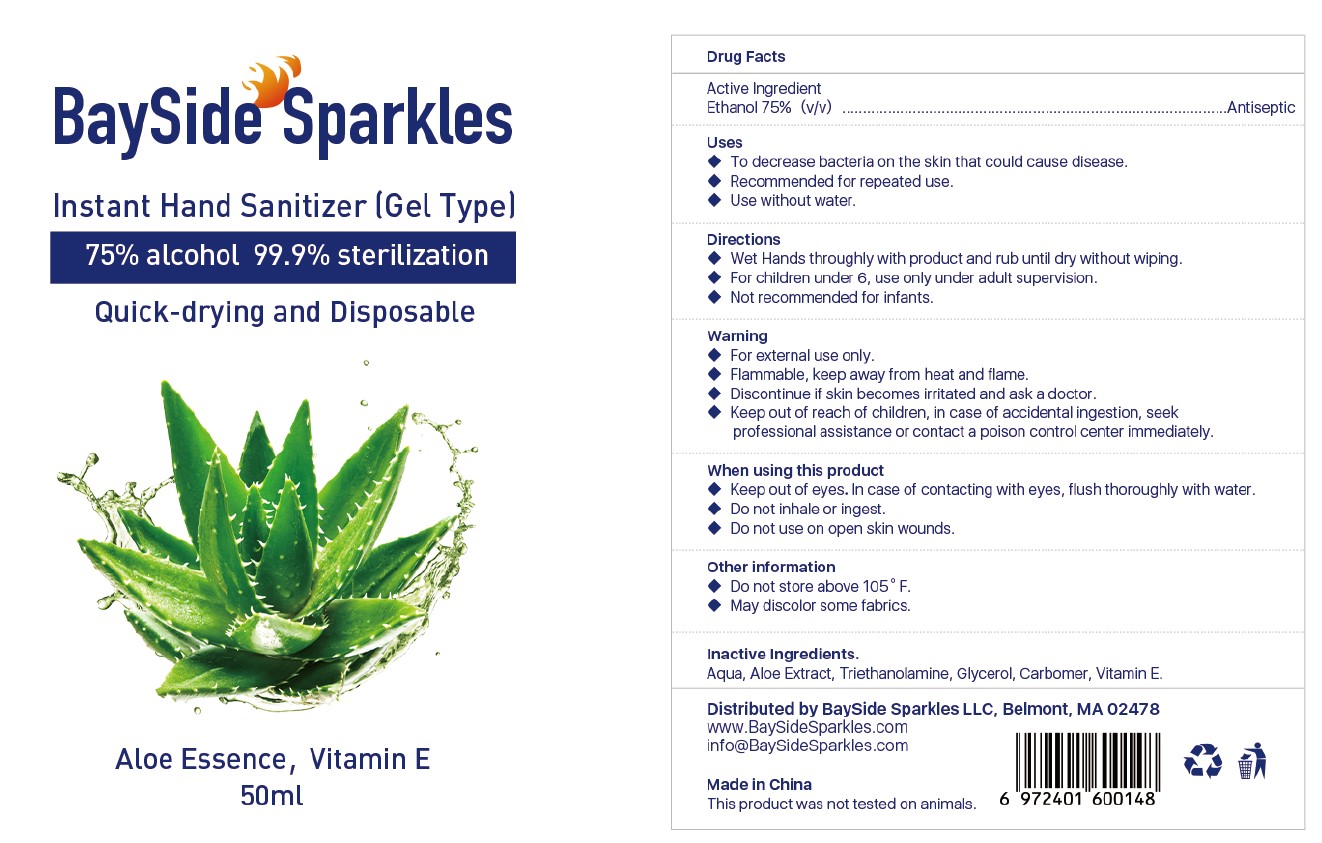 DRUG LABEL: Instant Hand Sanitizer
NDC: 77573-002 | Form: GEL
Manufacturer: JIANGSU AIMEILI COSMETIC CO.,LTD
Category: otc | Type: HUMAN OTC DRUG LABEL
Date: 20240105

ACTIVE INGREDIENTS: ALCOHOL 75 mL/100 mL
INACTIVE INGREDIENTS: ALPHA-TOCOPHEROL 1 mL/100 mL; ALOE VERA LEAF 2 mL/100 mL; GLYCERIN 0.1 mL/100 mL; CARBOMER HOMOPOLYMER, UNSPECIFIED TYPE 0.25 mL/100 mL; WATER; TROLAMINE 0.25 mL/100 mL; HYDANTOIN 0.2 mL/100 mL

77573-002 nstant hand sanitizer

Active Ingredient(s)

ethanol 75% (v/v) Purpose: Antiseptic

Purpose

Antiseptic

Use

to decrease bacteria on the skin that could cause disease

recommended for repeated use

use without water

Warnings

For external use only.

Flammable. Keep away from heat or flame

discontinue if skin becomes irritated and ask a doctor

keep out of reach of children, in case of accodental igestion,seek prefessional assistance or contact a poison control center immediately

do not inhale or ingest

do not use on open skin wounds.

when using this product

keep out of eyes.In case of contacting with eyes,flush thoroughly with water.

do not inhale or ingest

do not use on open skin wounds

STOP USE

discontine of skin becomes irritated and ask a doctor.

Keep out of reach of children,in case of accidental ingestion,seek professional assistance or contact a poison control center immediately

Keep out of reach of children. in case of accidental ingestion,seek professional assistance or contact a poison control center immediately.

Directions

wet hands thoughly with product and rub until dry without wiping

for children under 6,use only under adult supervision

not recommended for infants

Other information

do not store above 105℉

may discolor some fabrics

Inactive ingredients

Aqua,Aloe extract, triethanolamine,glycerin,carbomer,vitamin E